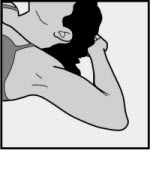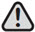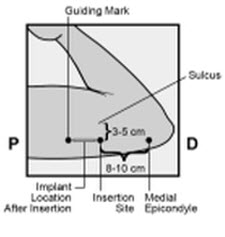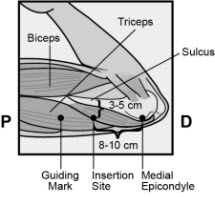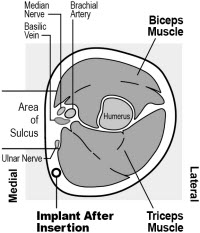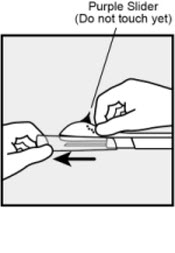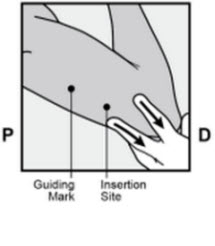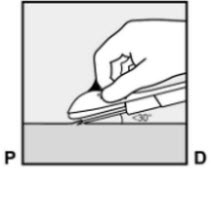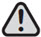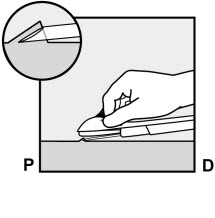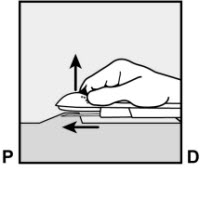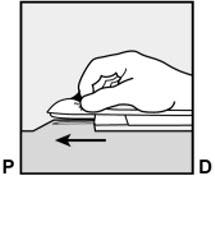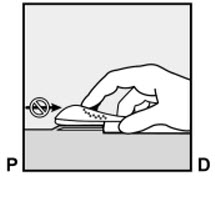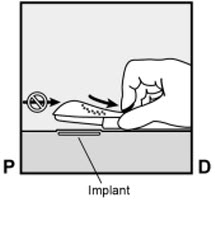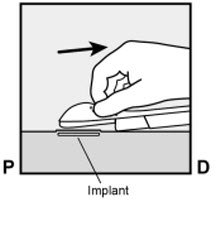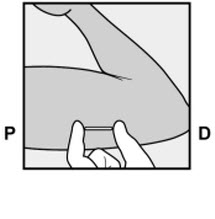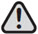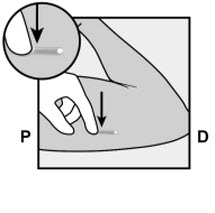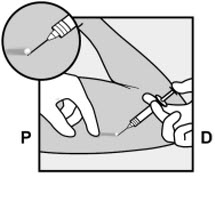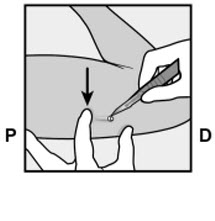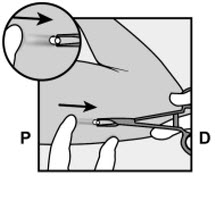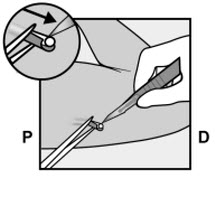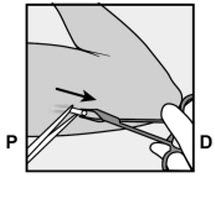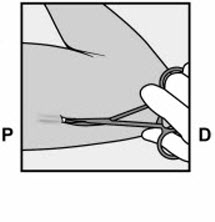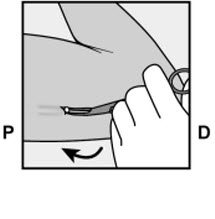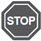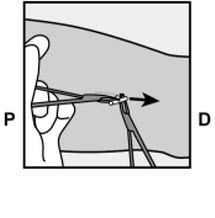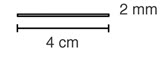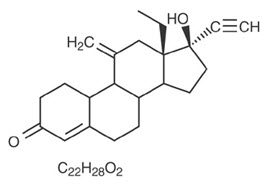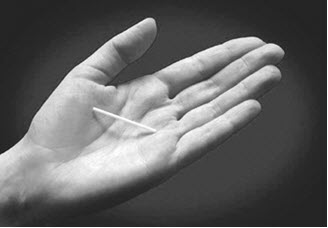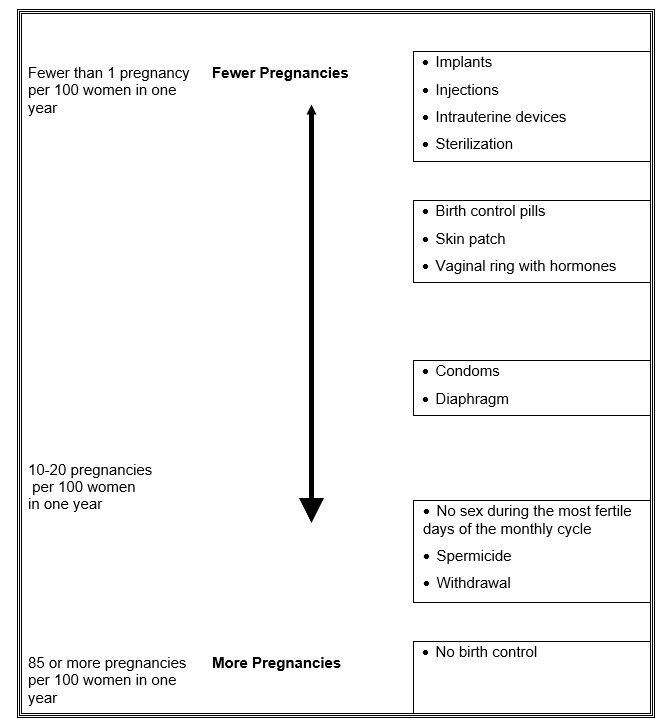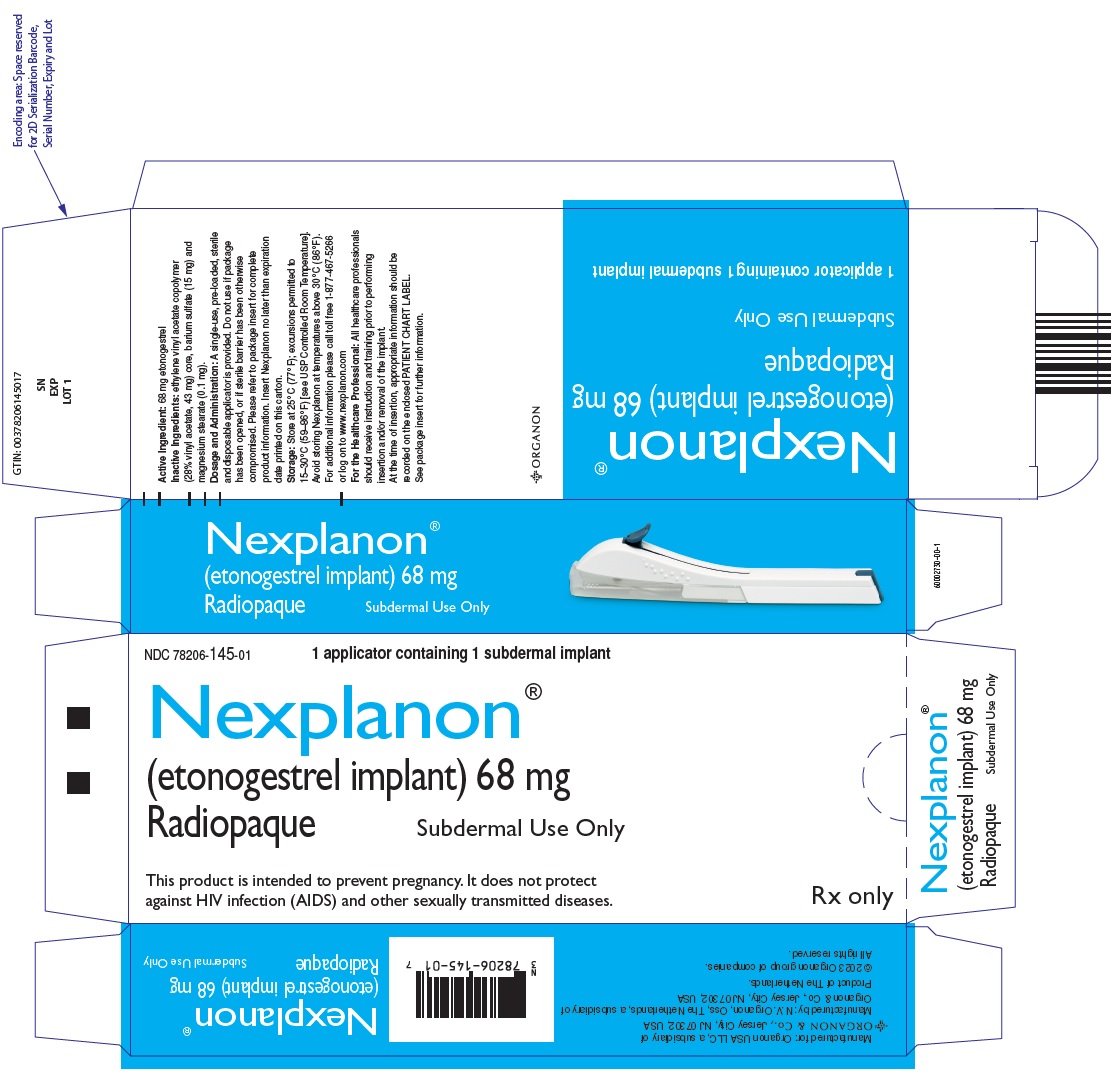 DRUG LABEL: Nexplanon
NDC: 78206-145 | Form: IMPLANT
Manufacturer: Organon LLC
Category: prescription | Type: HUMAN PRESCRIPTION DRUG LABEL
Date: 20260116

ACTIVE INGREDIENTS: ETONOGESTREL 68 mg/1 1
INACTIVE INGREDIENTS: BARIUM SULFATE 15 mg/1 1; MAGNESIUM STEARATE 0.1 mg/1 1; ETHYLENE-VINYL ACETATE COPOLYMER (28% VINYL ACETATE) 43 mg/1 1

HIGHLIGHTS OF PRESCRIBING INFORMATION

These highlights do not include all the information needed to use NEXPLANON safely and effectively. See full prescribing information for NEXPLANON.
NEXPLANON® (etonogestrel implant), for subdermal use
Radiopaque
Initial U.S. Approval: 2001

WARNING: RISK OF COMPLICATIONS DUE TO IMPROPER INSERTION and REMOVAL

- Improper insertion of NEXPLANON increases the risk of complications [see Warnings and Precautions (5.1)].
- Proper training prior to first use of NEXPLANON can minimize the risk of improper NEXPLANON insertion [see Warnings and Precautions (5.1)].
- NEXPLANON is available only through a restricted program under a Risk Evaluation and Mitigation Strategy (REMS) called the NEXPLANON REMS [see Warnings and Precautions (5.2)].

RECENT MAJOR CHANGES

Indications and Usage (1) | 01/2026
Dosage and Administration (2) | 01/2026
Warnings and Precautions (5.1, 5.2) | 01/2026

1 INDICATIONS AND USAGE

NEXPLANON is a progestin indicated for prevention of pregnancy in women of reproductive potential for up to 5 years. (1)

2 DOSAGE AND ADMINISTRATION

Insert one NEXPLANON subdermally just under the skin at the inner side of the non-dominant upper arm. NEXPLANON must be removed no later than by the end of the fifth year. (2)

3 DOSAGE FORMS AND STRENGTHS

NEXPLANON consists of a single, radiopaque, rod-shaped implant, containing 68 mg etonogestrel, pre-loaded in the needle of a disposable applicator. (3)

4 CONTRAINDICATIONS

- Known or suspected pregnancy. (4)
- Current or past history of thrombosis or thromboembolic disorders. (4, 5.5)
- Liver tumors, benign or malignant, or active liver disease. (4, 5.8)
- Undiagnosed abnormal uterine bleeding. (4, 5.3)
- Known or suspected breast cancer, personal history of breast cancer, or other progestin-sensitive cancer, now or in the past. (4, 5.7)
- Allergic reaction to any of the components of NEXPLANON. (4, 6)

5 WARNINGS AND PRECAUTIONS

- Insertion and removal complications: Pain, paresthesia, bleeding, hematoma, scarring, infection, or migration to vasculature, including pulmonary vessels, may occur. Symptoms associated with implants in pulmonary vessels include chest pain, dyspnea, cough, or hemoptysis. Surgical interventions may be necessary to remove implants. (5.1)
- Menstrual bleeding pattern: Counsel women regarding changes in bleeding frequency, intensity, or duration. (5.3)
- Ectopic pregnancies: Be alert to the possibility of an ectopic pregnancy in women using NEXPLANON who become pregnant or complain of lower abdominal pain. (5.4)
- Thrombotic and other vascular events: The NEXPLANON implant should be removed in the event of a thrombosis. (5.5)
- Liver disease: Remove the NEXPLANON implant if jaundice occurs. (5.8)
- Elevated blood pressure: The NEXPLANON implant should be removed if blood pressure rises significantly and becomes uncontrolled. (5.10)
- Carbohydrate and lipid metabolic effects: Monitor prediabetic and diabetic women using NEXPLANON. (5.12)

6 ADVERSE REACTIONS

Most common (≥10%) adverse reactions reported in clinical trials were change in menstrual bleeding pattern, headache, vaginitis, weight increase, acne, breast pain, abdominal pain, and pharyngitis. (6.1)

To report SUSPECTED ADVERSE REACTIONS, contact Organon USA LLC, a subsidiary of Organon & Co., at 1-844-674-3200 or FDA at 1-800-FDA-1088 or www.fda.gov/medwatch.

7 DRUG INTERACTIONS

Drugs or herbal products that induce certain enzymes, such as CYP3A4, may decrease the effectiveness of progestin hormonal contraceptives or increase breakthrough bleeding. (7.1)

8 USE IN SPECIFIC POPULATIONS

- Pregnancy: Discontinue if maintaining a pregnancy. (8.1)

FULL PRESCRIBING INFORMATION

WARNING: RISK OF COMPLICATIONS DUE TO IMPROPER INSERTION and REMOVAL

- Improper insertion of NEXPLANON increases the risk of complications [see Warnings and Precautions (5.1)].
- Proper training prior to first use of NEXPLANON can minimize the risk of improper NEXPLANON insertion [see Warnings and Precautions (5.1)].
- Because of the risk of complications due to improper insertion and removal NEXPLANON is available only through a restricted program under a Risk Evaluation and Mitigation Strategy (REMS) called the NEXPLANON REMS [see Warnings and Precautions (5.2)].

1 INDICATIONS AND USAGE

NEXPLANON® is indicated for prevention of pregnancy in women of reproductive potential for up to 5 years.

2 DOSAGE AND ADMINISTRATION

The efficacy of NEXPLANON does not depend on daily, weekly, or monthly administration.

All healthcare professionals should receive instruction and training prior to performing insertion and/or removal of NEXPLANON.

A single NEXPLANON implant is inserted subdermally just under the skin at the inner side of the non-dominant upper arm. The insertion site is overlying the triceps muscle about 8-10 cm (3-4 inches) from the medial epicondyle of the humerus and 3-5 cm (1.25-2 inches) posterior to (below) the sulcus (groove) between the biceps and triceps muscles. This location is intended to avoid the large blood vessels and nerves lying within and surrounding the sulcus (see Figures 2a, 2b and 2c). Inserting an implant more deeply than subdermally (a deep insertion) may preclude palpation and localization, making removal difficult or impossible [see Dosage and Administration (2.3) and Warnings and Precautions (5.1)].

NEXPLANON must be inserted by the expiration date stated on the packaging. NEXPLANON is a long-acting (up to 5 years), reversible, hormonal contraceptive method. The implant must be removed by the end of the fifth year and may be replaced by a new implant at the time of removal, if continued contraceptive protection is desired.

2.1 Initiating Contraception with NEXPLANON

IMPORTANT: Rule out pregnancy before inserting the implant.

Timing of insertion depends on the woman's recent contraceptive history, as follows:

• No preceding hormonal contraceptive use in the past month

NEXPLANON should be inserted between Day 1 (first day of menstrual bleeding) and Day 5 of the menstrual cycle, even if the woman is still bleeding.

If inserted as recommended, back-up contraception is not necessary. If deviating from the recommended timing of insertion, the woman should be advised to use a barrier method until 7 days after insertion. If intercourse has already occurred, pregnancy should be excluded.

• Switching contraceptive method to NEXPLANON

Combination hormonal contraceptives:

NEXPLANON should preferably be inserted on the day after the last active tablet of the previous combined oral contraceptive or on the day of removal of the vaginal ring or transdermal patch. At the latest, NEXPLANON should be inserted on the day following the usual tablet-free, ring-free, patch-free or placebo tablet interval of the previous combined hormonal contraceptive.

If inserted as recommended, back-up contraception is not necessary. If deviating from the recommended timing of insertion, the woman should be advised to use a barrier method until 7 days after insertion. If intercourse has already occurred, pregnancy should be excluded.

Progestin-only contraceptives:

There are several types of progestin-only methods. NEXPLANON should be inserted as follows:

- Injectable Contraceptives: Insert NEXPLANON on the day the next injection is due.
- Minipill: A woman may switch to NEXPLANON on any day of the month. NEXPLANON should be inserted within 24 hours after taking the last tablet.
- Contraceptive implant or intrauterine system (IUS): Insert NEXPLANON on the same day the previous contraceptive implant or IUS is removed.

If inserted as recommended, back-up contraception is not necessary. If deviating from the recommended timing of insertion, the woman should be advised to use a barrier method until 7 days after insertion. If intercourse has already occurred, pregnancy should be excluded.

• Following abortion or miscarriage

- First Trimester: NEXPLANON should be inserted within 5 days following a first trimester abortion or miscarriage.
- Second Trimester: Insert NEXPLANON between 21 to 28 days following second trimester abortion or miscarriage.

If inserted as recommended, back-up contraception is not necessary. If deviating from the recommended timing of insertion, the woman should be advised to use a barrier method until 7 days after insertion. If intercourse has already occurred, pregnancy should be excluded.

• Postpartum

- Not Breastfeeding: NEXPLANON should be inserted between 21 to 28 days postpartum. If inserted as recommended, back-up contraception is not necessary. If deviating from the recommended timing of insertion, the woman should be advised to use a barrier method until 7 days after insertion. If intercourse has already occurred, pregnancy should be excluded.
- Breastfeeding: NEXPLANON should not be inserted until after the fourth postpartum week. The woman should be advised to use a barrier method until 7 days after insertion. If intercourse has already occurred, pregnancy should be excluded.

2.2 Insertion of NEXPLANON

The basis for successful use and subsequent removal of NEXPLANON is a correct and carefully performed subdermal insertion of the single, rod-shaped implant in accordance with the instructions. Both the healthcare professional and the woman should be able to feel the implant under the skin after placement.

All healthcare professionals performing insertions and/or removals of NEXPLANON must receive instructions and training prior to inserting or removing the implant.

Preparation

Before inserting NEXPLANON, complete training which includes carefully reading the instructions for insertion as well as the full prescribing information [see Warnings and Precautions (5.2)]. If you are unsure of the necessary steps to safely insert and/or remove NEXPLANON, do not attempt the procedure.

Call the Organon Service Center at 1-844-674-3200 if you have any questions. Videos demonstrating insertion and removal are available online for trained healthcare professionals (www.NEXPLANONREMS.com).

Before insertion of NEXPLANON, the healthcare professional should confirm that:

- The woman is not pregnant and has no other contraindication for the use of NEXPLANON [see Contraindications (4)].
- The woman has had a medical history and physical examination, including a gynecologic examination, performed.
- The woman understands the benefits and risks of NEXPLANON.
- The woman has received a copy of the Patient Labeling included in packaging.
- The woman does not have allergies to the antiseptic and anesthetic to be used during insertion.

Insert NEXPLANON under aseptic conditions.

The following equipment is needed for the implant insertion:

- An examination table for the woman to lie on
- Sterile surgical drapes, sterile gloves, antiseptic solution, surgical marker
- Local anesthetic, needles, and syringe
- Sterile gauze, adhesive bandage, pressure bandage

Insertion Procedure

To help make sure the implant is inserted just under the skin, the healthcare professionals should be positioned to see the advancement of the needle by viewing the applicator from the side and not from above the arm. From the side view, the insertion site and the movement of the needle just under the skin can be clearly visualized.

For illustrative purposes, Figures depict the left inner arm.

Step 1. Have the woman lie on her back on the examination table with her non-dominant arm flexed at the elbow and externally rotated so that her hand is underneath her head (or as close as possible) (Figure 1).

Figure 1

Step 2. Identify the insertion site, which is at the inner side of the non-dominant upper arm. The insertion site is overlying the triceps muscle about 8-10 cm (3-4 inches) from the medial epicondyle of the humerus and 3-5 cm (1.25-2 inches) posterior to (below) the sulcus (groove) between the biceps and triceps muscles (Figures 2a, 2b and 2c). This location is intended to avoid the large blood vessels and nerves lying within and surrounding the sulcus. If it is not possible to insert the implant in this location (e.g., in women with thin arms), it should be inserted as far posterior from the sulcus as possible. [See Warnings and Precautions (5.1).]

Step 3. Make two marks with a surgical marker: first, mark the spot where the etonogestrel implant will be inserted, and second, mark a spot at 5 centimeters (2 inches) proximal (toward the shoulder) to the first mark (Figure 2a and 2b). This second mark (guiding mark) will later serve as a direction guide during insertion.

Figure 2a
P – Proximal (toward the shoulder)
D – Distal (toward the elbow)

Figure 2b

Figure 2c: Cross section of the upper left arm, as viewed from the elbow
Medial (inner side of the arm)
Lateral (outer side of the arm)

Step 4. After marking the arm, confirm the site is in the correct location on the inner side of the arm.

Step 5. Clean the skin from the insertion site to the guiding mark with an antiseptic solution.

Step 6. Anesthetize the insertion area (for example, with anesthetic spray or by injecting 2 mL of 1% lidocaine just under the skin along the planned insertion tunnel).

Step 7. Remove the sterile preloaded disposable NEXPLANON applicator containing the implant from its blister packaging. Prior to use, visually inspect the packaging for breaches of integrity or damage (e.g., torn, punctured, etc.). If the packaging has any visual damage that could compromise sterility, do not use the product.

Step 8. Hold the applicator just above the needle at the textured surface area. Remove the transparent protection cap by sliding it horizontally in the direction of the arrow away from the needle (Figure 3). If the cap does not come off easily, the applicator should not be used. You should see the white colored implant by looking into the tip of the needle. Do not touch the purple slider until you have fully inserted the needle subdermally, as doing so will retract the needle and prematurely release the implant from the applicator.

Step 9. If the purple slider is released prematurely, restart the procedure with a new applicator.

Figure 3

Step 10. With your free hand, stretch the skin around the insertion site towards the elbow (Figure 4).

Figure 4

Step 11. The implant should be inserted subdermally just under the skin [see Warnings and Precautions (5.1)].

To help make sure the implant is inserted just under the skin, you should position yourself to see the advancement of the needle by viewing the applicator from the side and not from above the arm. From the side view (see Figure 6), you can clearly see the insertion site and the movement of the needle just under the skin.

Step 12. Puncture the skin with the tip of the needle slightly angled less than 30° (Figure 5a).

Figure 5a

Step 13. Insert the needle until the bevel (slanted opening of the tip) is just under the skin (and no further) (Figure 5b). If you inserted the needle deeper than the bevel, withdraw the needle until only the bevel is beneath the skin.

Figure 5b

Step 14. Lower the applicator to a nearly horizontal position. To facilitate subdermal placement, lift the skin with the needle while sliding the needle to its full length (Figure 6). You may feel slight resistance but do not exert excessive force. If the needle is not inserted to its full length, the implant will not be inserted properly.

If the needle tip emerges from the skin before needle insertion is complete, the needle should be pulled back and be readjusted to subdermal position before completing the insertion procedure.

Figure 6

Step 15. Keep the applicator in the same position with the needle inserted to its full length (Figure 7). If needed, you may use your free hand to stabilize the applicator. Unlock the purple slider by pushing it slightly down (Figure 8a). Move the slider fully back until it stops. Do not move the applicator while moving the purple slider (Figure 8b). The implant is now in its final subdermal position, and the needle is locked inside the body of the applicator. The applicator can now be removed (Figure 8c).

Figure 7

Figure 8a

Figure 8b

Figure 8c

If the applicator is not kept in the same position during this procedure or if the purple slider is not moved fully back until it stops, the implant will not be inserted properly and may protrude from the insertion site.

If the implant is protruding from the insertion site, remove the implant and perform a new procedure at the same insertion site using a new applicator. Do not push the protruding implant back into the incision.

Step 16. Apply a small adhesive bandage over the insertion site.

Step 17. Always verify the presence of the implant in the woman's arm immediately after insertion by palpation. By palpating both ends of the implant, you should be able to confirm the presence of the 4 cm rod (Figure 9). See "If the rod is not palpable after insertion" below.

Figure 9

Step 18. Request that the woman palpate the implant.

Step 19. Apply a pressure bandage with sterile gauze to minimize bruising. The woman may remove the pressure bandage in 24 hours and the small adhesive bandage over the insertion site after 3 to 5 days.

Step 20. Complete the PATIENT CHART LABEL and affix it to the woman's medical record.

Step 21. The applicator is for single use only and should be disposed in accordance with the Center for Disease Control and Prevention guidelines for handling of hazardous waste.

If the rod is not palpable after insertion:

If you cannot feel the implant or are in doubt of its presence, the implant may not have been inserted or it may have been inserted deeply:

- Check the applicator. The needle should be fully retracted and only the purple tip of the obturator should be visible.
- Use other methods to confirm the presence of the implant. Given the radiopaque nature of the implant, suitable methods for localization are two-dimensional X-ray and X-ray computerized tomography (CT scan). Ultrasound scanning (USS) with a high-frequency linear array transducer (10 MHz or greater) or magnetic resonance imaging (MRI) may be used. If these methods fail, call the Organon Service Center at 1-844-674-3200 for information on the procedure for measuring etonogestrel blood levels which can be used for verification of the presence of the implant.

Until the presence of the implant has been verified, the woman should be advised to use a non-hormonal contraceptive method, such as condoms.

Deeply-placed implants should be localized and removed as soon as possible to avoid the potential for distant migration [see Warnings and Precautions (5.1)].

2.3 Removal of NEXPLANON

Preparation

Removal of the implant should only be performed under aseptic conditions by a healthcare professional who is familiar with the removal technique. If you are unfamiliar with the removal technique, call 1-844-674-3200 for further information.

Before initiating the removal procedure, the healthcare professional should assess the location of the implant and carefully read the instructions for removal. The exact location of the implant in the arm should be verified by palpation. If the implant is not palpable, consult the medical record to verify the arm which contains the implant. If the implant cannot be palpated, it may be deeply located or have migrated. Consider that it may lie close to vessels and nerves. Removal of non-palpable implants should only be performed by a healthcare professional experienced in removing deeply placed implants and familiar with localizing the implant and the anatomy of the arm. Call 1-844-674-3200 for further information. [See Localization and Removal of a Non-Palpable Implant, below.]

Procedure for Removal of an Implant that is Palpable

Before removal of the implant, the healthcare professional should confirm that:

- The woman does not have allergies to the antiseptic or anesthetic to be used.

The following equipment is needed for removal of the implant:

- An examination table for the woman to lie on
- Sterile surgical drapes, sterile gloves, antiseptic solution, surgical marker
- Local anesthetic, needles, and syringe
- Sterile scalpel, forceps (straight and curved mosquito)
- Skin closure, sterile gauze, and pressure bandage

Removal Procedure

For illustrative purposes, Figures depict the left inner arm

Step 1. Have the woman lie on her back on the table. The arm should be positioned with the elbow flexed and the hand underneath the head (or as close as possible). (See Figure 1.)

Step 2. Locate the implant by palpation. Push down the end of the implant closest to the shoulder (Figure 10) to stabilize it; a bulge should appear indicating the tip of the implant that is closest to the elbow. If the tip does not pop up, removal of the implant may be more challenging and should be performed by professionals experienced with removing deeper implants. Call 1-844-674-3200 for further information.

Mark the distal end (end closest to the elbow), for example, with a surgical marker.

Figure 10
P – Proximal (toward the shoulder)
D – Distal (toward the elbow)

Step 3. Clean the site with an antiseptic solution.

Step 4. Anesthetize the site, for example, with 0.5 to 1 mL 1% lidocaine, where the incision will be made (Figure 11). Be sure to inject the local anesthetic under the implant to keep the implant close to the skin surface. Injection of local anesthetic over the implant may make removal more difficult.

Figure 11

Step 5. Push down the end of the implant closest to the shoulder (Figure 12) to stabilize it throughout the procedure. Starting over the tip of the implant closest to the elbow, make a longitudinal (parallel to the implant) incision of 2 mm towards the elbow. Take care not to cut the tip of the implant.

Figure 12

Step 6. The tip of the implant should pop out of the incision. If it does not, gently push the implant towards the incision until the tip is visible. Grasp the implant with forceps and, if possible, remove the implant (Figure 13). If needed, gently remove adherent tissue from the tip of the implant using blunt dissection. If the implant tip is not exposed following blunt dissection, make an incision into the tissue sheath and then remove the implant with the forceps (Figures 14 and 15).

Figure 13

Figure 14

Figure 15

Step 7. If the tip of the implant does not become visible in the incision, insert forceps (preferably curved mosquito forceps, with the tips pointed up) superficially into the incision (Figure 16). Gently grasp the implant and then flip the forceps over into your other hand (Figure 17).

Figure 16

Figure 17

Step 8. With a second pair of forceps carefully dissect the tissue around the implant and grasp the implant (Figure 18). The implant can then be removed. If the implant cannot be grasped, stop the procedure and refer the woman to a healthcare professional experienced with complex removals or call 1-844-674-3200.

Figure 18

Step 9. Confirm that the entire implant, which is 4 cm long, has been removed by measuring its length. There have been reports of broken implants while in the patient's arm. In some cases, difficult removal of the broken implant has been reported. If a partial implant (less than 4 cm) is removed, the remaining piece should be removed by following the instructions in section 2.3. If the woman would like to continue using NEXPLANON, a new implant may be inserted immediately after the old implant is removed using the same incision as long as the site is in the correct location [see Dosage and Administration (2.4)].

Step 10. After removing the implant, close the incision with a sterile adhesive wound closure.

Step 11. Apply a pressure bandage with sterile gauze to minimize bruising. The woman may remove the pressure bandage in 24 hours and the sterile adhesive wound closure in 3 to 5 days.

Localization and Removal of a Non-Palpable Implant

There have been reports of migration of the implant; usually this involves minor movement relative to the original position [see Warnings and Precautions (5.1)], but may lead to the implant not being palpable at the location in which it was placed. An implant that has been deeply inserted or has migrated may not be palpable and therefore imaging procedures, as described below, may be required for localization.

A non-palpable implant should always be located prior to attempting removal. Given the radiopaque nature of the implant, suitable methods for localization include two-dimensional X-ray and X-ray computer tomography (CT). Ultrasound scanning (USS) with a high-frequency linear array transducer (10 MHz or greater) or magnetic resonance imaging (MRI) may be used. Once the implant has been localized in the arm, the implant should be removed by a healthcare professional experienced in removing deeply placed implants and familiar with the anatomy of the arm. The use of ultrasound guidance during the removal should be considered.

If the implant cannot be found in the arm after comprehensive localization attempts, consider applying imaging techniques to the chest as events of migration to the pulmonary vasculature have been reported. If the implant is located in the chest, surgical or endovascular procedures may be needed for removal; healthcare professionals familiar with the anatomy of the chest should be consulted.

If at any time these imaging methods fail to locate the implant, etonogestrel blood level determination can be used for verification of the presence of the implant. For details on etonogestrel blood level determination, call 1-844-674-3200 for further instructions.

If the implant migrates within the arm, removal may require a minor surgical procedure with a larger incision or a surgical procedure in an operating room. Removal of deeply-inserted implants should be conducted with caution to help prevent injury to deeper neural or vascular structures in the arm. Non-palpable and deeply-inserted implants should be removed by healthcare professionals familiar with the anatomy of the arm and removal of deeply-inserted implants.

Exploratory surgery without knowledge of the exact location of the implant is strongly discouraged.

2.4 Replacing NEXPLANON

Immediate replacement can be done after removal of the previous implant and is similar to the insertion procedure described in section 2.2 Insertion of NEXPLANON.

The new implant may be inserted in the same arm, and through the same incision from which the previous implant was removed, if the site is in the correct location, i.e., 8-10 cm from the medial epicondyle of the humerus and 3-5 cm posterior to (below) the sulcus [see Dosage and Administration (2.2)]. If the same incision is being used to insert a new implant, anesthetize the insertion site [for example, 2 mL lidocaine (1%)] applying it just under the skin along the 'insertion canal.'

Follow the subsequent steps in the insertion instructions [see Dosage and Administration (2.2)].

3 DOSAGE FORMS AND STRENGTHS

Single, white/off-white, soft, radiopaque, flexible, ethylene vinyl acetate (EVA) copolymer implant, 4 cm in length and 2 mm in diameter containing 68 mg etonogestrel, 15 mg of barium sulfate, and 0.1 mg of magnesium stearate.

4 CONTRAINDICATIONS

NEXPLANON should not be used in women who have

- Known or suspected pregnancy
- Current or past history of thrombosis or thromboembolic disorders
- Liver tumors, benign or malignant, or active liver disease
- Undiagnosed abnormal uterine bleeding
- Known or suspected breast cancer, personal history of breast cancer, or other progestin-sensitive cancer, now or in the past
- Allergic reaction to any of the components of NEXPLANON [see Adverse Reactions (6)]

5 WARNINGS AND PRECAUTIONS

The following information is based on experience with the etonogestrel implants (IMPLANON and/or NEXPLANON), other progestin-only contraceptives, or experience with combination (estrogen plus progestin) oral contraceptives.

5.1 Risk of Complications Due to Improper Insertion and Removal

Complications of Insertion and Removal

NEXPLANON should be inserted subdermally so that it will be palpable after insertion, and this should be confirmed by palpation immediately after insertion. Failure to insert NEXPLANON properly may go unnoticed unless it is palpated immediately after insertion. Undetected failure to insert the implant may lead to an unintended pregnancy. Complications related to insertion and removal procedures may occur, e.g., pain, paresthesia, bleeding, hematoma, scarring, or infection.

If NEXPLANON is inserted deeply (intramuscular or intrafascial), neural or vascular injury may occur. To help reduce the risk of neural or vascular injury, NEXPLANON should be inserted subdermally just under the skin at the inner side of the non-dominant upper arm overlying the triceps muscle, about 8-10 cm (3-4 inches) from the medial epicondyle of the humerus, and 3-5 cm (1.25-2 inches) posterior to (below) the sulcus (groove) between the biceps and triceps muscles. This location is intended to avoid the large nerves and blood vessels lying within and surrounding the sulcus. Deep insertions of NEXPLANON have been associated with paresthesia (due to neural injury), migration of the implant (due to intramuscular or fascial insertion), and intravascular insertion. If infection develops at the insertion site, start suitable treatment. If the infection persists, the implant should be removed. Incomplete insertions or infections may lead to expulsion.

Reports of implant migration within the arm may have been related to deep insertion. Postmarketing reports of implants located within the vessels of the arm and the pulmonary artery also may have been related to deep insertions or intravascular insertions. Some cases of implants found within the pulmonary artery were associated with chest pain and/or respiratory disorders (such as dyspnea, cough, or hemoptysis); others were asymptomatic. In cases where the implant has migrated to the pulmonary artery, endovascular or surgical procedures may be needed for removal.

Implant removal may be difficult or impossible if the implant is not inserted correctly, is inserted too deeply, not palpable, encased in fibrous tissue, or has migrated. If at any time the implant cannot be palpated, it should be localized, and removal is recommended. When an implant is removed, it is important to remove it in its entirety [see Dosage and Administration (2.3)].

Exploratory surgery without knowledge of the exact location of the implant is strongly discouraged. Removal of deeply inserted implants should be conducted with caution in order to prevent injury to deeper neural or vascular structures in the arm and be performed by healthcare professionals familiar with the anatomy of the arm. If the implant is located in the chest, healthcare professionals familiar with the anatomy of the chest should be consulted. Failure to remove the implant may result in continued effects of etonogestrel, such as compromised fertility, ectopic pregnancy, or persistence or occurrence of a drug-related adverse event.

Broken or Bent Implants

Cases of breakage or bending of implants while inserted within a patient’s arm have been reported. Cases of migration of a broken implant fragment within the arm have also occurred. These cases may be related to external forces, e.g., manipulation of the implant or contact sports. The release rate of etonogestrel may be slightly increased in a broken or bent implant, based on in vitro data. As noted previously, when an implant is removed, it is important to remove it in its entirety [see Dosage and Administration (2.3)].

NEXPLANON is available only through a restricted program under a REMS [see Warnings and Precautions (5.2)].

5.2 NEXPLANON REMS

NEXPLANON is only available through a restricted program under a REMS called NEXPLANON REMS because of the risk of complications due to improper insertion and removal [see Warnings and Precautions (5.1)].

Notable requirements of the NEXPLANON REMS include the following:

- Healthcare providers must be certified with the program by enrolling and completing training on the proper insertion and removal of NEXPLANON prior to first use.
- Pharmacies must be certified with the program and must only dispense NEXPLANON to certified healthcare providers who dispense NEXPLANON for insertion.
- Wholesalers and distributors must be registered with the program and must only distribute to certified pharmacies and certified healthcare providers.

Further information is available at www.NEXPLANONREMS.com and 1-833-697-7367.

5.3 Changes in Menstrual Bleeding Patterns

After starting NEXPLANON, women are likely to have a change from their normal menstrual bleeding pattern. These may include changes in bleeding frequency (absent, less, more frequent or continuous), intensity (reduced or increased) or duration. In clinical trials of the non-radiopaque etonogestrel implant (IMPLANON), bleeding patterns ranged from amenorrhea (1 in 5 women) to frequent and/or prolonged bleeding (1 in 5 women). The bleeding pattern experienced during the first three months of NEXPLANON use is broadly predictive of the future bleeding pattern for many women. Women should be counseled regarding the bleeding pattern changes they may experience so that they know what to expect. Abnormal bleeding should be evaluated as needed to exclude pathologic conditions or pregnancy.

In clinical studies of the non-radiopaque etonogestrel implant, reports of changes in bleeding pattern were the most common reason for stopping treatment (11.1%). Irregular bleeding (10.8%) was the single most common reason women stopped treatment, while amenorrhea (0.3%) was cited less frequently. In these studies, women had an average of 17.7 days of bleeding or spotting every 90 days (based on 3,315 intervals of 90 days recorded by 780 patients). The percentages of patients having 0, 1-7, 8-21, or >21 days of spotting or bleeding over a 90-day interval while using the non-radiopaque etonogestrel implant are shown in Table 1.

Table 1: Bleeding or Spotting: Incidence and Duration Over a 90-Day Interval While Using the Non-Radiopaque Etonogestrel Implant (IMPLANON)
Total Days of Bleeding or Spotting | Percentage of Patients
Total Days of Bleeding or Spotting | Treatment Days 91-180 (N = 745) | Treatment Days 271-360 (N = 657) | Treatment Days 631-720 (N = 547)
0 Days | 19% | 24% | 17%
1-7 Days | 15% | 13% | 12%
8-21 Days | 30% | 30% | 37%
>21 Days | 35% | 33% | 35%

Bleeding patterns observed with use of the non-radiopaque etonogestrel implant for up to 2 years, and the proportion of 90-day intervals with these bleeding patterns, are summarized in Table 2.

Table 2: Bleeding Patterns Using the Non-Radiopaque Etonogestrel Implant (IMPLANON) During the First 2 Years of Use [Based on 3315 recording periods of 90 days duration in 780 women, excluding the first 90 days after implant insertion]
BLEEDING PATTERNS | DEFINITIONS | % [% = Percentage of 90-day intervals with this pattern]
Infrequent | Less than three bleeding and/or spotting episodes in 90 days (excluding amenorrhea) | 33.6
Amenorrhea | No bleeding and/or spotting in 90 days | 22.2
Prolonged | Any bleeding and/or spotting episode lasting more than 14 days in 90 days | 17.7
Frequent | More than 5 bleeding and/or spotting episodes in 90 days | 6.7

In case of undiagnosed, persistent, or recurrent abnormal vaginal bleeding, appropriate measures should be conducted to rule out malignancy.

5.4 Ectopic Pregnancies

As with all progestin-only contraceptive products, be alert to the possibility of an ectopic pregnancy among women using NEXPLANON who become pregnant or complain of lower abdominal pain. Although ectopic pregnancies are uncommon among women using NEXPLANON, a pregnancy that occurs in a woman using NEXPLANON may be more likely to be ectopic than a pregnancy occurring in a woman using no contraception.

5.5 Thrombotic and Other Vascular Events

The use of combination hormonal contraceptives (progestin plus estrogen) increases the risk of vascular events, including arterial events (strokes and myocardial infarctions) or deep venous thrombotic events (venous thromboembolism, deep venous thrombosis, retinal vein thrombosis, and pulmonary embolism). NEXPLANON is a progestin-only contraceptive. It is unknown whether this increased risk is applicable to etonogestrel alone. It is recommended, however, that women with risk factors known to increase the risk of venous and arterial thromboembolism be carefully assessed.

There have been postmarketing reports of serious arterial thrombotic and venous thromboembolic events, including cases of pulmonary emboli (some fatal), deep vein thrombosis, myocardial infarction, and strokes, in women using etonogestrel implants. NEXPLANON should be removed in the event of a thrombosis.

Due to the risk of thromboembolism associated with pregnancy and immediately following delivery, NEXPLANON should not be used prior to 21 days postpartum. Women with a history of thromboembolic disorders should be made aware of the possibility of a recurrence.

Evaluate for retinal vein thrombosis immediately if there is unexplained loss of vision, proptosis, diplopia, papilledema, or retinal vascular lesions.

Consider removal of the NEXPLANON implant in case of long-term immobilization due to surgery or illness.

5.6 Ovarian Cysts

If follicular development occurs, atresia of the follicle is sometimes delayed, and the follicle may continue to grow beyond the size it would attain in a normal cycle. Generally, these enlarged follicles disappear spontaneously. On rare occasion, surgery may be required.

5.7 Carcinoma of the Breast and Reproductive Organs

Women who currently have or have had breast cancer should not use hormonal contraception because breast cancer may be hormonally sensitive [see Contraindications (4)]. Some studies suggest that the use of combination hormonal contraceptives might increase the incidence of breast cancer; however, other studies have not confirmed such findings.

Some studies suggest that the use of combination hormonal contraceptives is associated with an increase in the risk of cervical cancer or intraepithelial neoplasia. However, there is controversy about the extent to which these findings are due to differences in sexual behavior and other factors.

Women with a family history of breast cancer or who develop breast nodules should be carefully monitored.

5.8 Liver Disease

Disturbances of liver function may necessitate the discontinuation of hormonal contraceptive use until markers of liver function return to normal. Remove NEXPLANON if jaundice develops.

Hepatic adenomas are associated with combination hormonal contraceptives use. An estimate of the attributable risk is 3.3 cases per 100,000 for combination hormonal contraceptives users. It is not known whether a similar risk exists with progestin-only methods like NEXPLANON.

The progestin in NEXPLANON may be poorly metabolized in women with liver impairment. Use of NEXPLANON in women with active liver disease or liver cancer is contraindicated [see Contraindications (4)].

5.9 Weight Gain

In clinical studies, mean weight gain in U.S. non-radiopaque etonogestrel implant (IMPLANON) users was 2.8 pounds after one year and 3.7 pounds after two years. How much of the weight gain was related to the non-radiopaque etonogestrel implant is unknown. In studies, 2.3% of the users reported weight gain as the reason for having the non-radiopaque etonogestrel implant removed.

5.10 Elevated Blood Pressure

Women with a history of hypertension-related diseases or renal disease should be discouraged from using hormonal contraception. For women with well-controlled hypertension, use of NEXPLANON can be considered. Women with hypertension using NEXPLANON should be closely monitored. If sustained hypertension develops during the use of NEXPLANON, or if a significant increase in blood pressure does not respond adequately to antihypertensive therapy, NEXPLANON should be removed.

5.11 Gallbladder Disease

Studies suggest a small increased relative risk of developing gallbladder disease among combination hormonal contraceptive users. It is not known whether a similar risk exists with progestin-only methods like NEXPLANON.

5.12 Carbohydrate and Lipid Metabolic Effects

Use of NEXPLANON may induce mild insulin resistance and small changes in glucose concentrations of unknown clinical significance. Carefully monitor prediabetic and diabetic women using NEXPLANON.

Women who are being treated for hyperlipidemia should be followed closely if they elect to use NEXPLANON. Some progestins may elevate LDL levels and may render the control of hyperlipidemia more difficult.

5.13 Depressed Mood

Women with a history of depressed mood should be carefully observed. Consideration should be given to removing NEXPLANON in patients who become significantly depressed.

5.14 Return to Ovulation

In clinical trials with the non-radiopaque etonogestrel implant (IMPLANON), the etonogestrel levels in blood decreased below sensitivity of the assay by one week after removal of the implant. In addition, pregnancies were observed to occur as early as 7 to 14 days after removal. Therefore, a woman should re-start contraception immediately after removal of the implant if continued contraceptive protection is desired.

5.15 Fluid Retention

Hormonal contraceptives may cause some degree of fluid retention. They should be prescribed with caution, and only with careful monitoring, in patients with conditions which might be aggravated by fluid retention. It is unknown if NEXPLANON causes fluid retention.

5.16 Contact Lenses

Contact lens wearers who develop visual changes or changes in lens tolerance should be assessed by an ophthalmologist.

5.17 Monitoring

A woman who is using NEXPLANON should have a yearly visit with her healthcare professional for a blood pressure check and for other indicated health care.

5.18 Drug-Laboratory Test Interactions

Sex hormone-binding globulin concentrations may be decreased for the first six months after NEXPLANON insertion followed by gradual recovery. Thyroxine concentrations may initially be slightly decreased followed by gradual recovery to baseline.

6 ADVERSE REACTIONS

The following adverse reactions reported with the use of hormonal contraception are discussed elsewhere in the labeling:

- Changes in Menstrual Bleeding Patterns [see Warnings and Precautions (5.3)]
- Ectopic Pregnancies [see Warnings and Precautions (5.4)]
- Thrombotic and Other Vascular Events [see Warnings and Precautions (5.5)]
- Liver Disease [see Warnings and Precautions (5.8)]

6.1 Clinical Trials Experience

Adverse reaction rates observed in the clinical trials of a drug cannot be directly compared to rates in the clinical trials of another drug and may not reflect the rates observed in practice, because clinical trials are conducted under widely varying conditions.

In clinical trials of three years duration involving 942 women who were evaluated for safety, change in menstrual bleeding patterns (irregular menses) was the most common adverse reaction causing discontinuation of use of the non-radiopaque etonogestrel implant (IMPLANON) (11.1% of women).

Adverse reactions that resulted in a rate of discontinuation of ≥1% are shown in Table 3.

Table 3: Adverse Reactions Leading to Discontinuation of Treatment in 1% or More of Subjects in 3-Year Clinical Trials of the Non-Radiopaque Etonogestrel Implant (IMPLANON)
Adverse Reactions | All Studies N = 942
Bleeding Irregularities [Includes "frequent", "heavy", "prolonged", "spotting", and other patterns of bleeding irregularity.] | 11.1%
Emotional Lability [Among US subjects (N=330), 6.1% experienced emotional lability that led to discontinuation.] | 2.3%
Weight Increase | 2.3%
Headache | 1.6%
Acne | 1.3%
Depression [Among US subjects (N=330), 2.4% experienced depression that led to discontinuation.] | 1.0%

Other adverse reactions that were reported by at least 5% of subjects in the non-radiopaque etonogestrel implant clinical trials are listed in Table 4.

Table 4: Common Adverse Reactions Reported by ≥5% of Subjects in 3-Year Clinical Trials with the Non-Radiopaque Etonogestrel Implant (IMPLANON)
Adverse Reactions | All Studies N = 942
Headache | 24.9%
Vaginitis | 14.5%
Weight increase | 13.7%
Acne | 13.5%
Breast pain | 12.8%
Abdominal pain | 10.9%
Pharyngitis | 10.5%
Leukorrhea | 9.6%
Influenza-like symptoms | 7.6%
Dizziness | 7.2%
Dysmenorrhea | 7.2%
Back pain | 6.8%
Emotional lability | 6.5%
Nausea | 6.4%
Pain | 5.6%
Nervousness | 5.6%
Depression | 5.5%
Hypersensitivity | 5.4%
Insertion site pain | 5.2%

In a clinical trial of NEXPLANON, in which investigators were asked to examine the implant site after insertion, implant site reactions were reported in 8.6% of women. Erythema was the most frequent implant site complication, reported during or shortly after insertion, occurring in 3.3% of subjects. Additionally, hematoma (3.0%), bruising (2.0%), pain (1.0%), and swelling (0.7%) were reported.

In a separate clinical trial to assess contraceptive efficacy and safety of NEXPLANON beyond 3 years, up to 5 years, where a total of 498 women were evaluated for safety, a similar adverse reaction profile was observed as in Years 1 through 3.The most frequently reported adverse reaction >5% related to NEXPLANON was intermenstrual bleeding (5.4%), Changes in menstrual bleeding patterns were the most frequently reported adverse reaction leading to discontinuation occurring in 4.0% of participants.

6.2 Postmarketing Experience

Adverse Reactions and Events from Postmarketing Study

Nexplanon Observational Risk Assessment Study (NORA)

A postmarketing prospective active surveillance study was conducted among 7,364 patients in the United States to characterize the frequency of insertion-, localization-, and removal-related events.

Implant Insertion

Insertion difficulty or an insertion-related event occurred in 2.6% of the study participants. The overall incidence of incorrect insertion (unrecognized non-insertion, partial insertion, and deep insertion), reported by healthcare professionals was 12.6 per 1,000 insertions (95% CI, 10.2, 15.5). Table 5 summarizes the types and frequencies of these incorrect insertions.

Table 5: Incorrect Insertion Types and Incidence Reported by Healthcare Professionals
Type of Incorrect Insertion Event | Number of Events [Total Insertion Procedures = 7,364] | Incidence per 1,000 Insertions (95% CI)
(Initially) Unrecognized Non-insertions | 1 | 0.1 (0.0-0.8)
Partial Insertions | 27 | 3.7 (2.4-5.3)
Deep Insertions | 65 | 8.8 (6.8-11.2)
Injury to nerve or blood vessel | 1 | 0.1 (0.0-0.8)
Implant located within muscle | 2 | 0.3 (0.0-1.0)
Implant located adjacent to fascial tissue | 56 | 7.6 (5.8-9.9)
Implant not palpable | 6 | 0.8 (0.3-1.8)

Implant Removal

Implant removal information from both healthcare professionals and patients was collected for 5,159 patients (70% of the study population). Of these patients, data were available from healthcare professionals regarding 4,373 removal procedures. Healthcare professionals reported removal-related difficulties or complications in 1.5% of removal procedures. Table 6 provides a summary.

Table 6: Removal-related Events Reported by Healthcare Professionals
Removal Related Events | Number of Events [Total Removal Procedures: N= 4,373] | Incidence per 1,000 Removals (95% CI)
Any Event [Limited to one event per removal procedure] | 60 | 13.7 (10.5-17.6)
Encased in Fibrotic Tissue | 29 | 6.6 (4.4-9.5)
Implant Too Deep | 11 | 2.5 (1.3-4.5)
Implant Migrated [Only local migrations within the arm reported] | 6 | 1.4 (0.5-3.0)
Multiple Attempts Required | 13 | 3.0 (1.6-5.1)
Other [Other included fragmented or bent implants, patient-related issues, wound care required, two incisions required, and difficulty identifying end of device.] | 14 | 3.2 (1.8-5.4)

At the time of implant removal, eighteen implants (0.4% of all localizations or removals) were not palpable by the healthcare professionals. Of these eighteen, eleven were localized and removed, and one was localized but left in situ. Removal was not attempted for six non-palpable implants due to underlying health conditions, administrative problems, or unspecified reasons.

There were no reports of implants having migrated more than a few centimeters from the insertion site and no reports of implants localized at a site other than the arm. No neurovascular injuries were reported by healthcare professionals.

Adverse Reactions Reported by Patients

Table 7 provides a summary of adverse reactions reported by patients at the time of implant insertion and after removal.

Table 7: Adverse Reactions Reported by Patients at Implant Insertion and after Removal
Patient Reported Adverse Reactions | At Insertion |  | After Removal
Patient Reported Adverse Reactions | N [Total Insertion Procedures: N = 7,364] | Incidence per 1000 insertions (95% CI) | N | Incidence per 1000 insertions (95% CI)
Any Event [Limited to one event per woman] | 49 | 6.7 (4.9-8.8) | 42 [Based on 3,447 questionnaires] | 5.7 (4.1-7.7)
Pins and Needles/Numbness (arm/hand/fingers) | 17 | 2.3 (1.4-3.7) | 24 | 3.3 (2.1-4.9)
Severe Pain | 10 | 1.4 (0.7-2.5) | 11 | 1.5 (0.8-2.7)
Altered Strength/Movement | 3 | 0.4 (0.1-1.2) | 8 | 1.1 (0.5-2.1)
Injury to Blood Vessels or Blood Clots in Arm [No blood clots were observed during the study] | 2 | 0.3 (0-1.0) | -- | --
Other [“Other” included localized or insertion site pain, soreness, tenderness, dermatological changes, itching, bruising, and infection, local migrations within the arm, and physical damage to the implant (e.g., fractured or bent implant).] | 22 | 3.0 (1.9-4.5) | 18 | 2.4 (1.5-3.9)

In summary, this prospective active surveillance study showed that the frequency of insertion-, localization-, and removal-related events is consistent with results previously reported from clinical trials.

Adverse Reactions from Postmarketing Spontaneous Reports

The following additional adverse reactions have been identified during post-approval use of IMPLANON and NEXPLANON. It is not possible to reliably estimate their frequency or establish a causal relationship to drug exposure because these reactions are reported voluntarily from a population of uncertain size.

Gastrointestinal disorders: constipation, diarrhea, flatulence, vomiting.

General disorders and administration site conditions: edema, fatigue, implant site reaction, pyrexia.

Immune system disorders: anaphylactic reactions.

Infections and infestations: rhinitis, urinary tract infection.

Investigations: clinically relevant rise in blood pressure, weight decreased.

Metabolism and nutrition disorders: increased appetite.

Musculoskeletal and connective tissue disorders: arthralgia, musculoskeletal pain, myalgia.

Nervous system disorders: convulsions, migraine, somnolence.

Pregnancy, puerperium and perinatal conditions: ectopic pregnancy.

Psychiatric disorders: anxiety, insomnia, libido decreased.

Renal and urinary disorders: dysuria.

Reproductive system and breast disorders: breast discharge, breast enlargement, ovarian cyst, pruritus genital, vulvovaginal discomfort.

Skin and subcutaneous tissue disorders: angioedema, aggravation of angioedema and/or aggravation of hereditary angioedema, alopecia, chloasma, hypertrichosis, pruritus, rash, seborrhea, urticaria.

Vascular disorders: hot flush.

Reported complications related to insertion or removal of the etonogestrel implants include vasovagal reactions (e.g., hypotension, dizziness, or syncope), bruising, slight local irritation, pain, itching, fibrosis at the implant site, paresthesia or paresthesia-like events, scarring, and abscesses. Implant expulsions and migrations also have been reported. In some cases, implants have migrated to the chest wall or into the vasculature, including the pulmonary artery. Some cases of implants migrating to the pulmonary artery presented with symptoms of chest pain and/or respiratory disorders (e.g., dyspnea, cough, or hemoptysis); other cases have been reported as asymptomatic. In-patient surgical interventions might be necessary when removing implants associated with complications [see Warnings and Precautions (5.1)].

7 DRUG INTERACTIONS

Consult the labeling of concurrently-used drugs to obtain further information about interactions with hormonal contraceptives or the potential for enzyme alterations.

7.1 Effects of Other Drugs on Hormonal Contraceptives

Substances decreasing the plasma concentrations of hormonal contraceptives (HCs) and potentially diminishing the efficacy of HCs:

Drugs or herbal products that induce certain enzymes, including cytochrome P450 3A4 (CYP3A4), may decrease the plasma concentrations of HCs and potentially diminish the effectiveness of HCs or increase breakthrough bleeding.

Some drugs or herbal products that may decrease the effectiveness of HCs include efavirenz, phenytoin, barbiturates, carbamazepine, bosentan, felbamate, griseofulvin, oxcarbazepine, rifampicin, topiramate, rifabutin, rufinamide, aprepitant, and products containing St. John's wort. Interactions between HCs and other drugs may lead to breakthrough bleeding and/or contraceptive failure. Counsel women to use an alternative non-hormonal method of contraception or a back-up method when enzyme inducers are used with HCs, and to continue back-up non-hormonal contraception for 28 days after discontinuing the enzyme inducer to ensure contraceptive reliability.

Substances increasing the plasma concentrations of HCs:

Co-administration of certain HCs and strong or moderate CYP3A4 inhibitors such as itraconazole, voriconazole, fluconazole, grapefruit juice, or ketoconazole may increase the serum concentrations of progestins, including etonogestrel.

Human Immunodeficiency Virus (HIV)/Hepatitis C Virus (HCV) protease inhibitors and non-nucleoside reverse transcriptase inhibitors:

Significant changes (increase or decrease) in the plasma concentrations of progestin have been noted in cases of co-administration with HIV protease inhibitors (decrease [e.g., nelfinavir, ritonavir, darunavir/ritonavir, (fos)amprenavir/ritonavir, lopinavir/ritonavir, and tipranavir/ritonavir] or increase [e.g., indinavir and atazanavir/ritonavir])/HCV protease inhibitors (decrease [e.g., boceprevir and telaprevir]) or with non-nucleoside reverse transcriptase inhibitors (decrease [e.g., nevirapine, efavirenz] or increase [e.g., etravirine]). These changes may be clinically relevant in some cases.

Consult the prescribing information of anti-viral and anti-retroviral concomitant medications to identify potential interactions.

7.2 Effects of Hormonal Contraceptives on Other Drugs

Hormonal contraceptives may affect the metabolism of other drugs. Consequently, plasma concentrations may either increase (for example, cyclosporine) or decrease (for example, lamotrigine). Consult the labeling of all concurrently-used drugs to obtain further information about interactions with hormonal contraceptives or the potential for enzyme alterations.

8 USE IN SPECIFIC POPULATIONS

8.1 Pregnancy

Risk Summary

NEXPLANON is contraindicated during pregnancy because there is no need for pregnancy prevention in a woman who is already pregnant [see Contraindications (4)]. Epidemiologic studies and meta-analyses have not shown an increased risk of genital or non-genital birth defects (including cardiac anomalies and limb-reduction defects) following maternal exposure to low dose CHCs prior to conception or during early pregnancy. No adverse development outcomes were observed in pregnant rats and rabbits with the administration of etonogestrel during organogenesis at doses of 315 or 781 times the anticipated human dose (60 µg/day) (see Data).

NEXPLANON should be removed if maintaining a pregnancy.

Data

Animal Data

Teratology studies have been performed in rats and rabbits using oral administration up to 315 and 781 times the human etonogestrel dose (based upon body surface) and revealed no evidence of fetal harm due to etonogestrel exposure.

8.2 Lactation

Risk Summary

Small amounts of contraceptive steroids and/or metabolites, including etonogestrel are present in human milk. No significant adverse effects have been observed in the production or quality of breast milk, or on the physical and psychomotor development of breastfed infants (see Data).

Hormonal contraceptives, including etonogestrel, can reduce milk production in breastfeeding mothers. This is less likely to occur once breastfeeding is well-established; however, it can occur at any time in some women. When possible, advise the nursing mother about both hormonal and non-hormonal contraceptive options, as steroids may not be the initial choice for these patients. The developmental and health benefits of breastfeeding should be considered along with the mother's clinical need for NEXPLANON and any potential adverse effects on the breastfed child from NEXPLANON or from the underlying maternal condition.

Data

The amount of etonogestrel contained within breast milk was measured in 38 lactating women who began using IMPLANON during the fourth to eighth week postpartum. The study evaluated Implanon versus another contraceptive, was not randomized and data were considered observational and exploratory; therefore, comparisons could not be made. Based on the findings of this study, during the first months after insertion of IMPLANON, when maternal blood levels of etonogestrel are highest, about 100 ng of etonogestrel may be ingested by the child per day based on an average daily milk ingestion of 658 mL. Based on daily milk ingestion of 150 mL/kg, the mean daily infant etonogestrel dose one month after insertion of IMPLANON is about 2.2% of the weight-adjusted maternal daily dose, or about 0.2% of the estimated absolute maternal daily dose. Adverse reactions were not observed in breastfed infants exposed to etonogestrel through breast milk. No adverse effects on the production or quality of breast milk were detected.

8.4 Pediatric Use

The safety and effectiveness of NEXPLANON have been established in women of reproductive potential. Safety and effectiveness of NEXPLANON are expected to be the same in postpubertal adolescents as in adult women.

NEXPLANON is not indicated before menarche.

8.5 Geriatric Use

This product has not been studied in women over 65 years of age and is not indicated in this population.

8.6 Hepatic Impairment

No studies were conducted to evaluate the effect of hepatic disease on the disposition of NEXPLANON. The use of NEXPLANON in women with active liver disease is contraindicated [see Contraindications (4)].

10 OVERDOSAGE

Overdosage may result if more than one implant is inserted. In case of suspected overdose, the implant should be removed.

11 DESCRIPTION

NEXPLANON is a radiopaque, progestin-only, soft, flexible implant preloaded in a sterile, disposable applicator for subdermal use. The implant is white/off-white, non-biodegradable and 4 cm in length with a diameter of 2 mm (see Figure 19). Each implant consists of an ethylene vinyl acetate (EVA) copolymer (28% vinyl acetate, 43 mg) core, containing 68 mg of the synthetic progestin etonogestrel, barium sulfate ((15 mg), radiopaque ingredient), and magnesium stearate (0.1 mg), surrounded by an EVA copolymer skin. Once inserted subdermally, the release rate is 60-75 mcg/day in week 5-6 and decreases to approximately 40-50 mcg/day at the end of the first year, and then to approximately 15-20 mcg/day at the end of the fifth year. NEXPLANON is a progestin-only contraceptive and does not contain estrogen. NEXPLANON is not made with natural rubber latex.

Figure 19 (Not to scale)

Etonogestrel [13-Ethyl-17-hydroxy-11-methylene-18,19-dinor-17α-pregn-4-en-20-yn-3-one], structurally derived from 19-nortestosterone, is the synthetic biologically active metabolite of the synthetic progestin desogestrel. It has a molecular weight of 324.46 and the following structural formula (Figure 20).

Figure 20

12 CLINICAL PHARMACOLOGY

12.1 Mechanism of Action

The contraceptive effect of NEXPLANON is achieved by suppression of ovulation, increased viscosity of the cervical mucus, and alterations in the endometrium.

12.2 Pharmacodynamics

Exposure-response relationships of NEXPLANON are unknown.

12.3 Pharmacokinetics

Absorption

After subdermal insertion of the etonogestrel implant, etonogestrel is released into the circulation and is approximately 100% bioavailable. Maximum serum concentrations were reached within the first two weeks after insertion and gradually decreased over time. Table 8 shows mean (± standard deviation) serum concentrations of etonogestrel after insertion of NEXPLANON.

Table 8: Etonogestrel serum concentrations after NEXPLANON insertion
 | Etonogestrel serum concentrations [pg/mL] Mean (±standard deviation)
Time after insertion | Study 34528 [NEXPLANON use duration: 3 years.] | Study MK-8415-060 [Subjects had used NEXPLANON for 3 years (± 2 weeks) at time of study enrollment.]
2 weeks | 1200 (± 604) | NA
1 year | 202 (± 55) | NA
2 years | 164 (± 58) | NA
3 years | 138 (± 43) | 143 (± 74)
4 years | NA | 123 (± 45)
5 years | NA | 111 (± 51)
NA = not available

Distribution

The apparent volume of distribution averages about 201 L. Etonogestrel is approximately 32% bound to sex hormone binding globulin (SHBG) and 66% bound to albumin in blood.

Metabolism

In vitro data shows that etonogestrel is metabolized in liver microsomes by the cytochrome P450 3A4 isoenzyme. The biological activity of etonogestrel metabolites is unknown.

Excretion

The elimination half-life of etonogestrel is approximately 25 hours. Excretion of etonogestrel and its metabolites, either as free steroid or as conjugates, is mainly in urine and to a lesser extent in feces. After removal of the implant, etonogestrel concentrations decreased below sensitivity of the assay by one week.

Specific Population

Women with Obesity

Pharmacokinetics of etonogestrel was evaluated in a clinical trial during the use of NEXPLANON from years 3 to 5. The median (range) body mass index (BMI) of 215 study treatment completers was 27.9 (17.4 to 63.9) kg/m^2 at baseline. Among the completers, 86 had a BMI ≥30 kg/m^2 and 23 had a BMI ≥40 kg/m^2. Mean etonogestrel serum concentrations were relatively lower in subjects with a BMI ≥30 kg/m^2 compared with those with a BMI <30 kg/m^2; the ratio of mean etonogestrel serum concentrations ranged from 0.76-0.88 during the use of NEXPLANON from years 3 to 5. There is a substantial overlap in etonogestrel serum concentration ranges between the two BMI categories ≥30 kg/m^2 versus <30 kg/m^2 (49.7-455 pg/mL versus 33-363 pg/mL, respectively, at 5 years).

13 NONCLINICAL TOXICOLOGY

13.1 Carcinogenesis, Mutagenesis, Impairment of Fertility

In a 24-month carcinogenicity study in male and female rats with subdermal implants releasing 10 and 20 mcg etonogestrel per day (equal to approximately 1.8-3.6 times the systemic steady state exposure in women using NEXPLANON), no drug-related carcinogenic potential was observed. Etonogestrel was not genotoxic in the in vitro Ames/Salmonella reverse mutation assay, the chromosomal aberration assay in Chinese hamster ovary cells or the in vivo mouse micronucleus test. Fertility in female rats returned after withdrawal from treatment.

14 CLINICAL STUDIES

14.1 Pregnancy

In clinical trials of up to 3 years duration that involved 923 subjects, 18-40 years of age at entry, and 1756 women-years of use with the non-radiopaque etonogestrel implant (IMPLANON), the total exposures expressed as 28-day cycle equivalents by study year were:

Year 1: 10,866 cycles

Year 2: 8,581 cycles

Year 3: 3,442 cycles

The clinical trials excluded women who:

- Weighed more than 130% of their ideal body weight
- Were chronically taking medications that induce liver enzymes

In the subgroup of women, 18-35 years of age at entry, 6 pregnancies during 20,648 cycles of use were reported. Two pregnancies occurred in each of Years 1, 2, and 3. Each conception was likely to have occurred shortly before or within 2 weeks after removal of the non-radiopaque etonogestrel implant. With these 6 pregnancies, the cumulative Pearl Index (PI) was 0.38 pregnancies per 100 women-years of use.

The contraceptive efficacy of NEXPLANON during use from 3 to 5 years was evaluated in a multicenter, single-arm, open-label study (NCT04626596) conducted in the United States. The trial enrolled women 18 to 35 years of age who had been using NEXPLANON for 36 months (±2 weeks) from the date of insertion at the time of enrollment. A total of 399 women were evaluated, having a mean age of 27 years.

Participants were 74.2% White, 16.8% Black/African American, 3.8% Asian, 1.3% American Indian or Alaska Native, 0.5% Native Hawaiian or Other Pacific Islander, and 3.5% multiple or missing races. The mean BMI was 29.4 kg/m^2 (range: 17.2-64.3 kg/m^2) and the mean weight was 78.7 kg (range: 40.8-180.8 kg). One hundred fifty-two participants (38.1%) had a BMI ≥30 kg/m^2, including 40 participants (10.0%) with BMI ≥40 kg/m^2.

The total exposures expressed as 28-day cycle equivalents by study year were:

Year 4: 4478 cycles

Year 5: 3274 cycles

No pregnancies were reported in years 4 and 5, with a PI of 0.0 (95% CI- 0.00, 0.69) pregnancies per 100 women-years of use.

14.2 Return to Ovulation

In clinical trials with the non-radiopaque etonogestrel implant (IMPLANON), the etonogestrel levels in blood decreased below sensitivity of the assay by one week after removal of the implant. In addition, pregnancies were observed to occur as early as 7 to 14 days after removal. Therefore, a woman should re-start contraception immediately after removal of the implant if continued contraceptive protection is desired.

14.3 Implant Insertion and Removal Characteristics

Out of 301 insertions of the NEXPLANON implant in a clinical trial, the mean insertion time (from the removal of the protection cap of the applicator until retraction of the needle from the arm) was 27.9 ± 29.3 seconds. After insertion, 300 out of 301 (99.7%) NEXPLANON implants were palpable that were placed by trained providers. The single, non-palpable implant was not inserted according to the instructions.

16 HOW SUPPLIED/STORAGE AND HANDLING

16.1 How Supplied

NEXPLANON is supplied as follows:

NDC 78206-145-01

One NEXPLANON package consists of a single implant containing 68 mg etonogestrel, 15 mg of barium sulfate and 0.1 mg of magnesium stearate that is 4 cm in length and 2 mm in diameter, which is pre-loaded in the needle of a disposable applicator. The sterile applicator containing the implant is packed in a blister pack.

16.2 Storage and Handling

Store NEXPLANON at 20ºC to 25ºC (68ºF to 77ºF); excursions permitted between 15ºC to 30ºC (59ºF to 86ºF) [see USP Controlled Room Temperature]. Avoid storing NEXPLANON at temperatures above 30ºC (86ºF).

17 PATIENT COUNSELING INFORMATION

Advise the patient to read the FDA-approved patient labeling (Patient Information).

- Advise women about the insertion and removal procedure of the NEXPLANON implant. Provide the woman with a copy of the Patient Labeling and ensure that she understands the information in the Patient Labeling before insertion and removal.
- Advise women to contact their healthcare professional immediately if, at any time, they are unable to palpate the implant.
- Advise women that NEXPLANON does not protect against HIV infection (AIDS) or other sexually transmitted diseases.
- Advise women that the use of NEXPLANON may be associated with changes in their normal menstrual bleeding patterns so that they know what to expect.
- MRI Safety Information: NEXPLANON is MR safe.

Manufactured for: Organon USA LLC, a subsidiary of
ORGANON & Co.,
Jersey City, NJ 07302, USA

Manufactured by: N.V. Organon, Oss, The Netherlands, a subsidiary of Organon & Co., Jersey City, NJ 07302, USA

For patent information: www.organon.com/our-solutions/patent/

© 2026 Organon group of companies. All rights reserved.

uspi-og8415-iptx-2601r003

FDA-Approved Patient Labeling

NEXPLANON® (etonogestrel implant)
Radiopaque
Subdermal Use Only

NEXPLANON® does not protect against HIV infection (the virus that causes AIDS) or other sexually transmitted diseases.

Read this Patient Information leaflet carefully before you decide if NEXPLANON is right for you. This information does not take the place of talking with your healthcare professional. If you have any questions about NEXPLANON, ask your healthcare professional.

What is NEXPLANON?

NEXPLANON is a hormone-releasing birth control implant for prevention of pregnancy for up to 5 years. The implant is a flexible plastic rod about the size of a matchstick that contains a progestin hormone called etonogestrel. It contains a small amount of barium sulfate (15 mg), so that the implant can be seen by X-ray, an ethylene vinyl acetate (EVA) copolymer (28% vinyl acetate, 43 mg) core, and magnesium stearate (0.1 mg). Your healthcare professional will insert the implant just under the skin of the inner side of your upper arm. You can use a single NEXPLANON implant for up to 5 years. NEXPLANON does not contain estrogen.

What if I need birth control for more than 5 years?

The NEXPLANON implant must be removed by the end of 5 years. Your healthcare professional can insert a new implant under your skin after taking out the old one if you choose to continue using NEXPLANON for birth control.

What if I change my mind about birth control and want to stop using NEXPLANON before 5 years?

Your healthcare professional can remove the implant at any time. You may become pregnant as early as the first week after removal of the implant. If you do not want to get pregnant after your healthcare professional removes the NEXPLANON implant, you should start another birth control method right away.

How does NEXPLANON work?

NEXPLANON prevents pregnancy in several ways. The most important way is by stopping the release of an egg from your ovary. NEXPLANON also thickens the mucus in your cervix and this change may keep sperm from reaching the egg. NEXPLANON also changes the lining of your uterus.

How well does NEXPLANON work?

When the NEXPLANON implant is placed correctly, your chance of getting pregnant is very low (less than 1 pregnancy per 100 women who use NEXPLANON for 1 year).

The following chart shows the chance of getting pregnant for women who use different methods of birth control. Each box on the chart contains a list of birth control methods that are similar in effectiveness. The most effective methods are at the top of the chart. The box on the bottom of the chart shows the chance of getting pregnant for women who do not use birth control and are trying to get pregnant.

Who should not use NEXPLANON?

Do not use NEXPLANON if you have any of the following conditions:

- Are pregnant or think you may be pregnant
- Have, or have had, blood clots, such as blood clots in your legs (deep vein thrombosis), lungs (pulmonary embolism), eyes (total or partial blindness), heart (heart attack), or brain (stroke)
- Liver disease or a liver tumor
- Unexplained vaginal bleeding
- Breast cancer or any other cancer that is sensitive to progestin (a female hormone), now or in the past
- An allergy to anything in NEXPLANON

Tell your healthcare professional if you have or have had any of the conditions listed above. Your healthcare professional can suggest a different method of birth control.

In addition, talk to your healthcare professional about using NEXPLANON if you have any of the following conditions:

- Diabetes
- High cholesterol or triglycerides
- Headaches
- Gallbladder or kidney problems
- A history of depressed mood
- High blood pressure
- An allergy to numbing medicines (anesthetics) or medicines used to clean your skin (antiseptics). These medicines will be used when the implant is placed into or removed from your arm.

Interaction with Other Medicines

Tell your healthcare professional about all the medicines you take, including prescription and over-the-counter medicines, vitamins, and herbal supplements. Using certain medicines with NEXPLANON, including those listed below, may make NEXPLANON less effective:

- aprepitant
- barbiturates
- bosentan
- carbamazepine
- felbamate
- griseofulvin
- oxcarbazepine
- phenytoin
- rifampin
- St. John's wort
- topiramate
- HIV medicines
- Hepatitis C Virus medicines

Ask your healthcare professional if you are not sure if your medicine is one listed above.

If you are taking medicines or herbal products that might make NEXPLANON less effective, you and your healthcare professional may decide to leave NEXPLANON in place; in that case, an additional non-hormonal contraceptive should be used. It is necessary to use the additional non-hormonal contraceptive for 28 days after stopping the medicine or herbal product because its effect on NEXPLANON may last that long.

When you are using NEXPLANON, tell all your healthcare professionals that you have NEXPLANON in place in your arm.

Magnetic Resonance Imaging (MRI) Safety Information

NEXPLANON is MRI safe.

How is the NEXPLANON implant placed and removed?

Your healthcare professional will place and remove the NEXPLANON implant using a minor surgical procedure in his or her office. The implant is placed just under the skin on the inner side of your non-dominant upper arm.

The timing of insertion is important. Your healthcare professional may take the following steps to guide timing of insertion:

- Perform a pregnancy test before inserting NEXPLANON
- Schedule the insertion at a specific time of your menstrual cycle (for example, within the first 5 days of your regular menstrual bleeding). If the implant is placed after the fifth day of menses, then you should use an additional contraceptive method (such as a condom) for the first 7 days after insertion.

Your healthcare professional will cover the site where NEXPLANON was placed with 2 bandages. A small bandage will be placed over the insertion site. A larger pressure bandage will be placed over the smaller bandage. Leave the larger pressure bandage on for 24 hours. Keep the smaller bandage clean, dry, and in place for 3 to 5 days.

Immediately after the NEXPLANON implant has been placed, you and your healthcare professional should check that the implant is in your arm by feeling for it.

If you cannot feel the implant immediately after insertion, the implant may not have been inserted, or it may have been inserted deeply. A deep insertion may cause problems with locating and removing the implant. When the healthcare professional has located the implant, it should be removed.

If at any time you cannot feel the NEXPLANON implant, contact your healthcare professional immediately and use a non-hormonal birth control method (such as condoms) until your healthcare professional confirms that the implant is in place. You may need special tests to check that the implant is in place or to help find the implant when it is time to take it out. If the implant cannot be found in the arm after a thorough search, your healthcare professional may use X-rays or other imaging methods on your chest.

Depending on the exact position of the implant, removal may be difficult and may require surgery.

Keep track of the date the implant is to be removed. Schedule an appointment with your healthcare professional to remove the implant on or before the removal date.

Be sure to have checkups as advised by your healthcare professional.

What are the most common side effects I can expect while using NEXPLANON?

• Changes in Menstrual Bleeding Patterns (Menstrual Periods)

The most common side effect of NEXPLANON is a change in your normal menstrual bleeding pattern. In studies, one out of ten women stopped using the implant because of an unfavorable change in their bleeding pattern. You may experience longer or shorter bleeding during your periods or have no bleeding at all. The time between periods may vary, and you may also have spotting in between periods.

Tell your healthcare professional right away if you have the following concerns:

- You think you may be pregnant
- Your menstrual bleeding is heavy and prolonged

The following additional frequent side effects also caused women to stop using the implant:

- Mood swings
- Depressed mood
- Weight gain
- Headache
- Acne

Other common side effects include the following conditions:

- Headache
- Vaginitis (inflammation of the vagina)
- Weight gain
- Acne
- Breast pain
- Viral infections such as sore throats or flu-like symptoms
- Stomach pain
- Painful periods
- Mood swings, nervousness, or depressed mood
- Back pain
- Nausea
- Dizziness
- Pain
- Pain at the site of insertion

Implants have been reported to be found in a blood vessel, including a blood vessel in the lung which can be associated with shortness of breath, cough and/or the coughing up of blood or blood-stained mucus.

These are not all the possible side effects of NEXPLANON. Call your doctor for medical advice about side effects. You may report side effects to the FDA at 1-800-FDA-1088.

What are the possible risks of using NEXPLANON?

• Problems with Insertion and Removal

The implant may not be actually in your arm due to a failed insertion. If this happens, you may become pregnant. Immediately after insertion, and with help from your healthcare professional, you should be able to feel the implant under your skin. If you can’t feel the implant, tell your healthcare professional.

Location and removal of the implant may be difficult or impossible because the implant is not where it should be. Special procedures, including surgery in the hospital, may be needed to remove the implant. If the implant is not removed, then the effects of NEXPLANON will continue for a longer time.

Implants have been found in the pulmonary artery (a blood vessel in the lung). If the implant cannot be found in the arm, your healthcare professional may use X-rays or other imaging methods on the chest. If the implant is located in the chest, surgery may be needed.

The following problems related to insertion and removal may also occur:

- Vasovagal reactions (such as a drop in blood pressure, dizziness, or fainting)
- Pain, irritation, swelling, or bruising at the insertion site
- Numbness and tingling at the insertion site
- Scarring, including a thick scar called a keloid around the insertion site
- Infection
- Scar tissue may form around the implant making it difficult to remove
- The implant may come out by itself. You may become pregnant if the implant comes out by itself. Use a back-up birth control method and call your healthcare professional right away if the implant comes out.
- The need for surgery in the hospital to remove the implant
- Injury to nerves or blood vessels in your arm
- The implant breaks, making removal difficult

• Ectopic Pregnancy

If you become pregnant while using NEXPLANON, you have a slightly higher chance that the pregnancy will be ectopic (occurring outside the womb) than do women who do not use birth control. Unusual vaginal bleeding or lower stomach (abdominal) pain may be a sign of ectopic pregnancy. Ectopic pregnancy is a medical emergency that often requires surgery. Ectopic pregnancies can cause serious internal bleeding, infertility, and even death. Call your healthcare professional right away if you think you are pregnant or have unexplained lower stomach (abdominal) pain.

• Ovarian Cysts

Cysts may develop on the ovaries and usually go away without treatment, but sometimes surgery is needed to remove them.

• Breast Cancer

It is not known whether NEXPLANON use changes a woman's risk for breast cancer. If you have breast cancer now, or have had it in the past, do not use NEXPLANON because some breast cancers are sensitive to hormones.

• Serious Blood Clots

NEXPLANON may increase your chance of serious blood clots, especially if you have other risk factors such as smoking. It is possible to die from a problem caused by a blood clot, such as a heart attack or a stroke.

Serious blood clots can occur within blood vessels of different parts of the body, including the following examples:

- Legs (deep vein thrombosis)
- Lungs (pulmonary embolism)
- Brain (stroke)
- Heart (heart attack)
- Eyes (total or partial blindness)

The risk of serious blood clots is increased in women who smoke. If you smoke and want to use NEXPLANON, you should quit. Your healthcare professional may be able to help.

Tell your healthcare professional at least 4 weeks before if you are going to have surgery or will need to be on bed rest. You have an increased chance of getting blood clots during surgery or bed rest.

• Other Risks

A few women who use birth control that contains hormones may get the following conditions:

- High blood pressure
- Gallbladder problems
- Rare cancerous or noncancerous liver tumors

• Broken or Bent Implant

Breakage or bending of the implant while it is in your arm may occur due to external forces (such as manipulation of the implant or contact sports). A broken implant may move from the insertion site. If you feel that the implant may have broken or bent while in your arm, contact your healthcare professional.

When should I call my healthcare professional?

Call your healthcare professional right away if you have any of the following conditions:

- Pain in your lower leg that does not go away
- Severe chest pain or heaviness in the chest
- Sudden shortness of breath, sharp chest pain, or coughing blood
- Symptoms of a severe allergic reaction, such as swollen face, tongue or throat; trouble breathing or swallowing
- Sudden severe headache unlike your usual headaches
- Weakness or numbness in your arm, leg, or trouble speaking
- Sudden partial or complete blindness
- Yellowing of your skin or whites of your eyes, especially with fever, tiredness, loss of appetite, dark colored urine, or light-colored bowel movements
- Severe pain, swelling, or tenderness in the lower stomach (abdomen)
- Lump in your breast
- Problems sleeping, lack of energy, tiredness, or you feel very sad
- Heavy menstrual bleeding

What if I become pregnant while using NEXPLANON?

You should see your healthcare professional right away if you think that you may be pregnant. It is important to remove the implant and make sure that the pregnancy is not ectopic (occurring outside the womb). Based on experience with other hormonal contraceptives, NEXPLANON is not likely to cause birth defects.

Can I use NEXPLANON when I am breastfeeding?

If you are breastfeeding your child, you may use NEXPLANON if 4 weeks have passed since you had your baby. A small amount of the hormone contained in NEXPLANON passes into your breast milk. The health of breast-fed children whose mothers were using the implant has been studied up to 3 years of age in a small number of children. No effects on the growth and development of the children were seen. If you are breastfeeding and want to use NEXPLANON, talk with your healthcare professional for more information.

General information about the safe and effective use of NEXPLANON

Medicines are sometimes prescribed for purposes other than those listed in a Patient Information leaflet. If you would like more information, talk with your healthcare professional. You can ask your healthcare professional for information about NEXPLANON that is written for healthcare professionals.

Manufactured for: Organon USA LLC, a subsidiary of
ORGANON & Co.,
Jersey City, NJ 07302, USA

Manufactured by: N.V. Organon, Oss, The Netherlands, a subsidiary of Organon & Co., Jersey City, NJ 07302, USA

For patent information: www.organon.com/our-solutions/patent/

© 2026 Organon group of companies. All rights reserved.

usppi-og8415-iptx-2601r003

For more information, go to www.nexplanon.com or call 1-844-674-3200.

This Patient Information has been approved by the U.S. Food and Drug Administration.

Revised: 01/2026

PRINCIPAL DISPLAY PANEL - 68 mg Implant Blister Pack Carton

NDC 78206-145-01
1 applicator containing 1 subdermal implant

Nexplanon®
(etonogestrel implant) 68 mg
Radiopaque
Subdermal Use Only

This product is intended to prevent pregnancy. It does not protect
against HIV infection (AIDS) and other sexually transmitted diseases.
Rx only